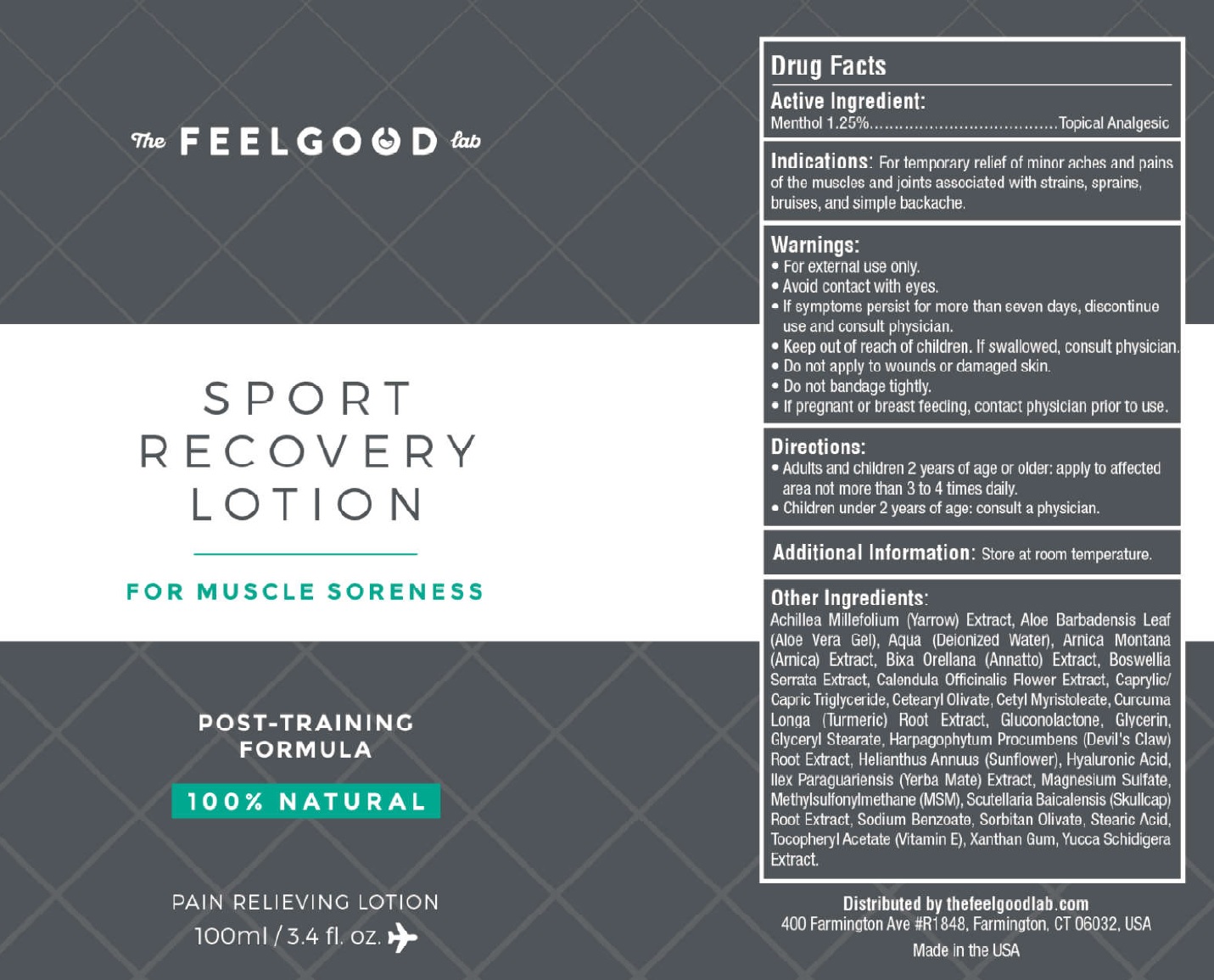 DRUG LABEL: FEEL GOOD LABS SPORT RECOVERY
NDC: 70554-291 | Form: LOTION
Manufacturer: THE FEEL GOOD LAB, LLC
Category: otc | Type: HUMAN OTC DRUG LABEL
Date: 20231105

ACTIVE INGREDIENTS: MENTHOL 12.5 mg/1 mL
INACTIVE INGREDIENTS: WATER; ARNICA MONTANA WHOLE; YELLOW WAX; INDIAN FRANKINCENSE; CALENDULA OFFICINALIS FLOWER; MEDIUM-CHAIN TRIGLYCERIDES; CETEARYL OLIVATE; CETYL MYRISTOLEATE; TURMERIC; GLUCONOLACTONE; GLYCERIN; GLYCERYL MONOSTEARATE; HARPAGOPHYTUM PROCUMBENS ROOT; HELIANTHUS ANNUUS FLOWERING TOP; HYALURONIC ACID; ILEX PARAGUARIENSIS LEAF; MAGNESIUM SULFATE, UNSPECIFIED FORM; DIMETHYL SULFONE; SCUTELLARIA BAICALENSIS ROOT; SODIUM BENZOATE; SORBITAN OLIVATE; STEARIC ACID; .ALPHA.-TOCOPHEROL ACETATE; XANTHAN GUM; YUCCA SCHIDIGERA WHOLE; ACHILLEA MILLEFOLIUM WHOLE; ALOE VERA LEAF; ANNATTO

FEEL GOOD LABS SPORT RECOVERY LOTION

Active Ingredient

Menthol 1.25%

PURPOSE

Topical analgesic

INDICATIONS

For the temporary relief of minor aches and pains of the muscles and joints associated with arthritis, simple backache.

WARNINGS

• For external use only. • Avoid contact with eyes. • If symptoms persist for more than seven days, discontinue use and consult physician.

Keep out of reach of children.

• If swallowed, consult physician.

• Do not apply to wounds or damaged skin. • Do not bandage tightly.

If pregnant or breastfeeding,

• consult physician prior to use.

DIRECTIONS

- Adults and children 2 years of age or older: Apply to affected area not more than 3 to 4 times daily.

- Children under 2 years of age: consult a physician.

ADDITIONAL INFORMATION

Store at room temperature.

OTHER INGREDIENTS

Achillea Millefolium (Yarrow) Extract, Aloe Barbadensis Leaf (Aloe Vera Gel), Annatto, Aqua (Deionized Water), Arnica Montana (Arnica) Extract, Bixa Orellana (Annatto) Extract, Boswellia Serrata Extract, Calendula Officinalis Flower Extract, Caprylic/Capric Triglyceride, Cetearyl Olivate, Cetyl Myristoleate, Curcuma Longa (Turmeric) Root Extract, Gluconolactone, Glycerin, Glyceryl Stearate, Harpagophytum Procumbens (Devil's Claw) Root Extract, Helianthus Annuus (Sunflower), Hyaluronic Acid, Ilex Paraguariensis (Yerba Mate) Extract, Magnesium Sulfate, Methylsulfonylmethane (MSM), Scutellaria Baicalensis (Skullcap) Root Extract, Sodium Benzoate, Sorbitan Olivate, Stearic Acid, Tocopheryl Acetate (Vitamin E), Xanthan Gum, Yucca Schidigera Extract